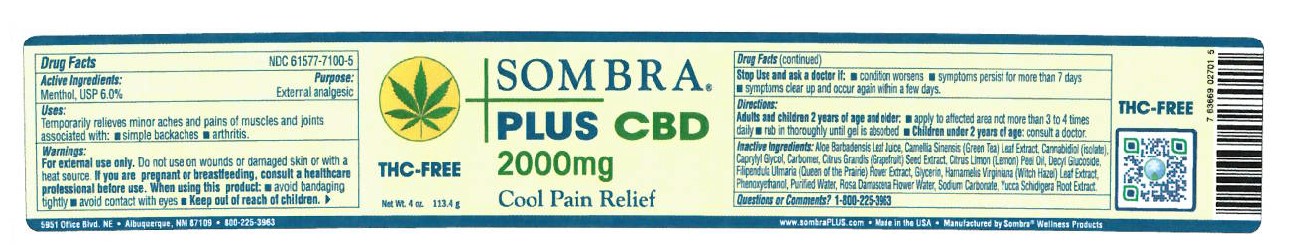 DRUG LABEL: SOMBRA PLUS CBD 2000MG COOL THERAPY
NDC: 61577-7101 | Form: GEL
Manufacturer: Sombra Cosmetics Inc.
Category: otc | Type: HUMAN OTC DRUG LABEL
Date: 20220524

ACTIVE INGREDIENTS: MENTHOL 0.06 g/1 g
INACTIVE INGREDIENTS: ALOE VERA LEAF; CARBOMER HOMOPOLYMER TYPE C; DECYL GLUCOSIDE; WATER; GRAPEFRUIT SEED OIL; GREEN TEA LEAF; FILIPENDULA ULMARIA FLOWER; ROSA CENTIFOLIA FLOWER OIL; SODIUM CARBONATE; GLYCERIN; WITCH HAZEL; YUCCA SCHIDIGERA ROOT; LEMON OIL; PHENOXYETHANOL; CAPRYLYL GLYCOL

Sombra Plux CBD 2000mg Cool Therapy

Active Ingredients

Menthol USP 6%

Purpose

External Analgesic

Keep out of reach of children

Uses

Temporarily relieves minor aches and pains of muscles and joints associated with: strains, bruises, and sprains

Warnings

For external use only. Do not use on wounds or damaged skin or with heat source. If you are pregnant or breastfeeding, consult a healthcare professional before use. When using this product: Avoid bandaging tightly, avoid contact with eyes, keep out of reach children

Directions

adults and children 2 years of age and older: apply to affected area not more than 3 to 4 times daily, rub in thoroughly until gel is absorbed, children under 2 years of age: consult a doctor.

Inactive Ingredients

aloe barbadensis leaf juice, camellia sinensis (green tea) leaf extract, Cannabidiol (isolate), caprylyl glycol, carbomer, citrus grandis (grapefruit) seed extract, citrus limon (lemon) peel oil, decyl glucoside, glycerin, hamamelis virginiana (witch hazel) leaf extract, phenoxyethanol, purified water, rosa damascena flower water, sodium carbonate, Filipendula ulmaria (queen of the prairie) flower extract, yucca schidigera root extract,